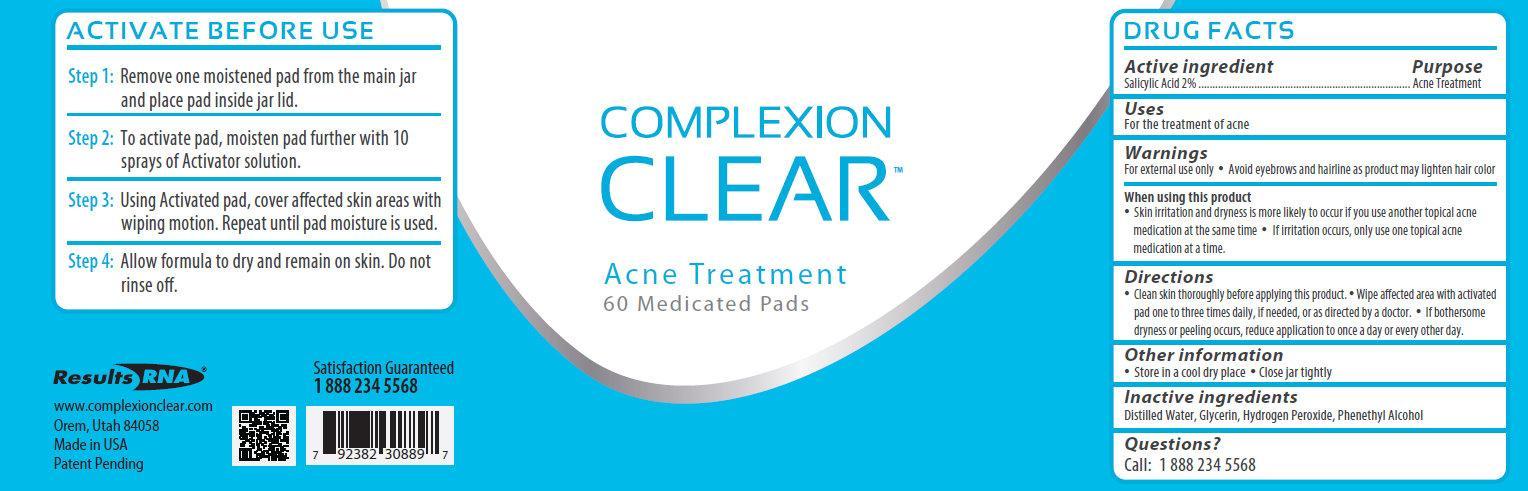 DRUG LABEL: COMPLEXION CLEAR ACNE TREATMENT
NDC: 42876-001 | Form: LIQUID
Manufacturer: Results RNA, LLC
Category: otc | Type: HUMAN OTC DRUG LABEL
Date: 20120809

ACTIVE INGREDIENTS: SALICYLIC ACID 2 mL/100 mL
INACTIVE INGREDIENTS: WATER; GLYCERIN; HYDROGEN PEROXIDE; PHENYLETHYL ALCOHOL

COMPLEXION CLEAR ACNE TREATMENT

ACTIVE INGREDIENT

Salicylic Acid 2%

PURPOSE

Acne Treatment

USES

For the treatment of acne

WARNINGS

For external use only

- Avoid eyebrows and hairline as product may lighten hair color

When using this product

- Skin irritation and dryness is more likely to occur if you use another topical acne medication at the same time.
- If irritation occurs, only use one topical acne medication at a time.

DIRECTIONS

- Clean skin thoroughly before applying this product
- Wipe affected area with activated pad one to three time daily, if needed, or as directed by a doctor.
- If bothersome dryness or peeling occurs, reduce application to once a day or every other day.

OTHER INFORMATION

- Store in a cool dry place
- Close jar tightly

INACTIVE INGREDIENTS

Distilled Water, Glycerin, Hydrogen Peroxide, Phenethyl Alcohol

Questions?

Call: 1 888 823 3869

ACTIVATE BEFORE USE

Step 1: Remove one moistened pad from the main jar and place pad inside jar lid.

Step 2: To activate pad, moisten pad further with 10 sprays of Activator solution.

Step 3: Using Activated pad, cover affected skin areas with wiping motion. Repeat until pad moisture is used.

Step 4: Allow formula to fry and remain on skin. Do not rinse off.

Results RNA

www.complexion clear.com

Orem, Utah 84058

Made in USA

Patent Pending

Satisfaction Guaranteed

1 888 823 3869

Complexion Clear Acne Treatment 60 pads (42876-001-60)

COMPLEXION

CLEAR

ACNE TREATMENT

60 MEDICATED PADS